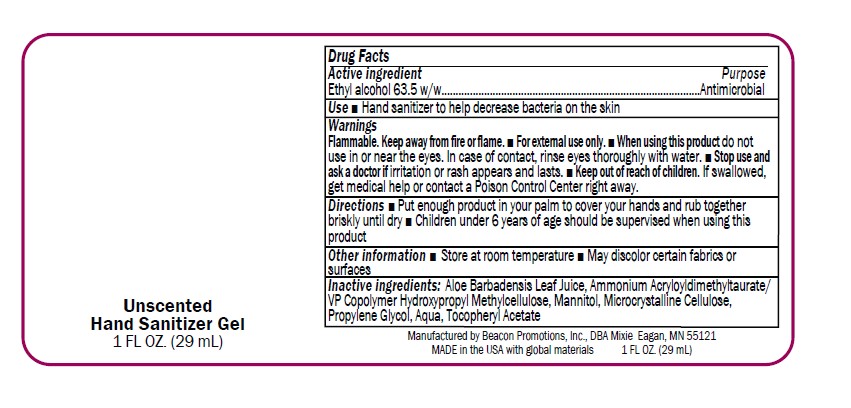 DRUG LABEL: Unscented Sanitizer
NDC: 70445-609 | Form: GEL
Manufacturer: Beacon Promotions, Inc.
Category: otc | Type: HUMAN OTC DRUG LABEL
Date: 20260112

ACTIVE INGREDIENTS: ALCOHOL 63.5 mL/100 mL
INACTIVE INGREDIENTS: PROPYLENE GLYCOL; AMMONIUM ACRYLOYLDIMETHYLTAURATE/VP COPOLYMER; ALOE VERA LEAF; WATER

Unscented Sanitizer

Drug Facts

Ethyl alcohol 63.5%

Put enough product in your palm to cover your hands and rub together briskly until dry

Purpose

Antimicrobial

Use

Antimicrobial

Warnings

Flammable. Keep away from fire or flame.

■ For external use only.

■ When using this product do not use in or near the eyes. In case of contact, rinse eyes thoroughly with water.

■ Stop use and ask a doctor if irritation or rash appears and lasts.

■ Keep out of reach of children. If swallowed, get medical help or contact a Poison Control Center right away.

Keep Out of Reach of Children

Directions

■ Put enough product in your palm to cover your hands and rub together briskly until dry

■ Children under 6 years of age should be supervised when using this product

Drug Facts

Ethyl alcohol 63.5% w/w

Inactive Ingredients

Inactive ingredients: Aloe Barbadensis Leaf Juice, Ammonium Acryloyldimethyltaurate/ VP Copolymer Hydroxypropyl Methylcellulose, Mannitol, Microcrystalline Cellulose, Propylene Glycol, Aqua, Tocopheryl Acetate

Other Information

■ Store at room temperature

■ May discolor certain fabrics or surfaces